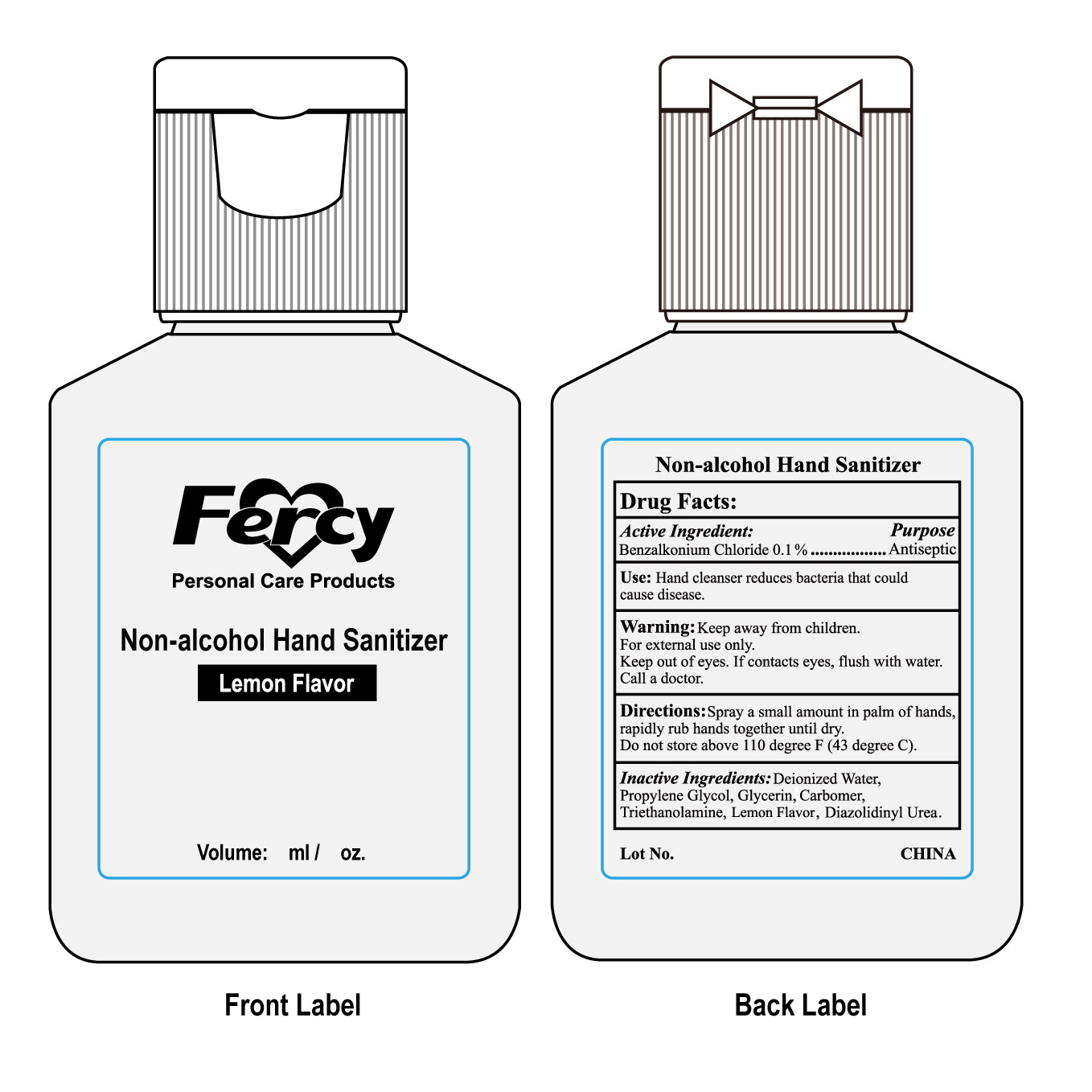 DRUG LABEL: NON ALCOHOL HAND SANITIZER
NDC: 50260-500 | Form: GEL
Manufacturer: Fercy Personal Care Products Co Limited
Category: otc | Type: HUMAN OTC DRUG LABEL
Date: 20101125

ACTIVE INGREDIENTS: Benzalkonium Chloride 0.1 mL/100 mL
INACTIVE INGREDIENTS: WATER 93.35 mL/100 mL; GLYCERIN 2 mL/100 mL; PROPYLENE GLYCOL 2 mL/100 mL; TROLAMINE 1 mL/100 mL; CARBOMER 934 0.9 mL/100 mL; Diazolidinyl Urea 0.15 mL/100 mL; LEMON 0.5 mL/100 mL

Fercy Personal Care Products NON ALCOHOL HAND SANITIZER Lemon Flavor

Active Ingredient

Benzalkonium Chloride 0.1%

PURPOSE

antiseptic

Use

Hand Cleanser reduces bacteria that could cause disease.

Warning

Keep away from children.
For external use only.
Keep out of eyes,if contacts eyes,flush with water .call a doctor

Directions

Spray a small amount in palm of hands,rapidly rub hands together until dry.
Do not store about 110 degree F(43 degree C)

Keep out of reach of children

Inactive Ingredients

DEIONIZED WATER、GLYCERIN、PROPYLENE GLYCOL、TRIETHANOLAMINE、CARBOMER、Lemon Flavor、Diazolidinyl Urea